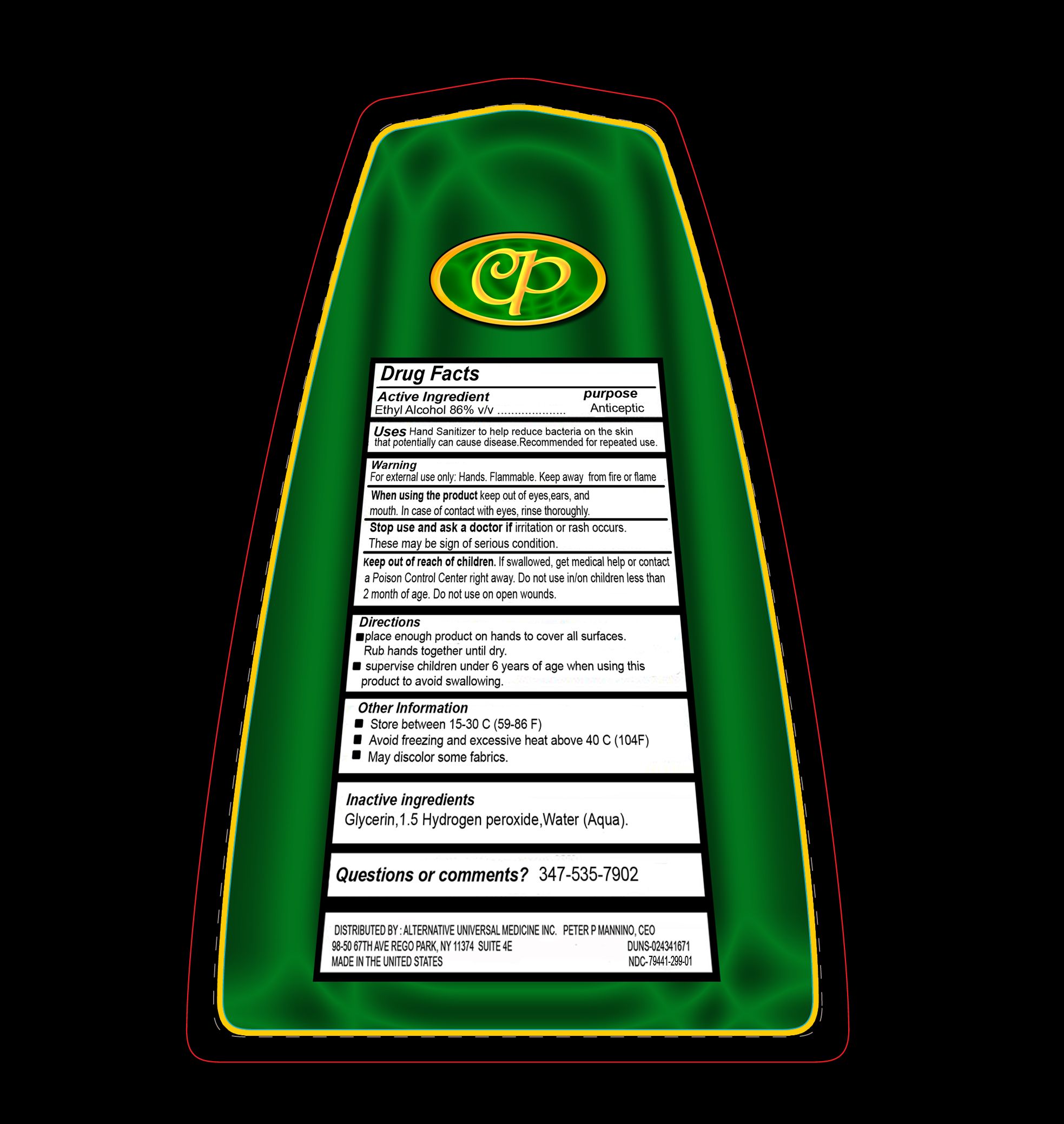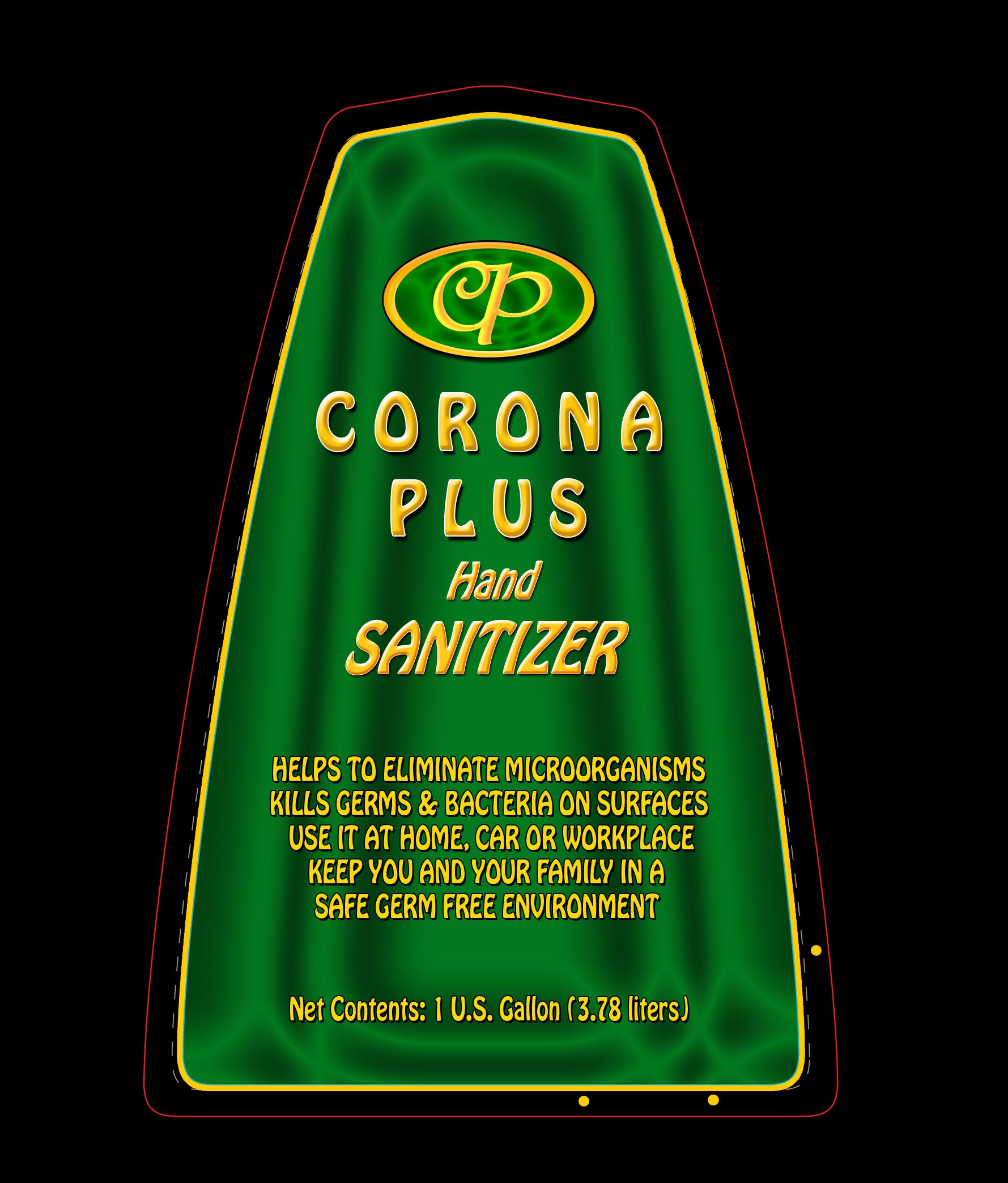 DRUG LABEL: Corona Plus
NDC: 79441-299 | Form: LIQUID
Manufacturer: ALTERNATIVE UNIVERSAL MEDICINE INC
Category: otc | Type: HUMAN OTC DRUG LABEL
Date: 20201027

ACTIVE INGREDIENTS: ALCOHOL 86.18 mL/100 mL
INACTIVE INGREDIENTS: GLYCERIN 4.17 mL/100 mL; HYDROGEN PEROXIDE 1.5 mL/100 mL; WATER 8.15 mL/100 mL

Coroa Plus Hand Sanitizer Registration

Product Application / Dosage

Place enough product on hands to cover all surfaces. Rub hands together until dry.

Keep out of reach of children. If swallowed, get medical help or contact a Poison Control Center right away. Do not use in/on children less than 2 month of age. Supervise children under 6 years of age when using this product to avoid swallowing.

Warnings Section

For external use only: hands. Flammable. Keep away from fire or flame. When using the product keep out of eyes, ears, and mouth. In case of contact with eyes, rinse thoroughly with water. Stop use and ask a doctor if irritation or rash occurs. These may be signs of serious condition. Keep out of reach of children. If swallowed, get medical help or contact a Poison Control Center right away. Do not use in/on children less than 2 month of age. Do not use on open wounds.

Inactive Ingredient Section

Inactive ingredients

Glycerin, Hydrogen peroxide, Purified water

Indication And Usage

Uses

Hand Sanitizer to help reduce bacteria on the skin that potentially can cause disease. Recommender for repeated use.

Warnings

For external use only: hands. Flammable. Keep away from fire or flame. When using the product keep out of eyes, ears, and mouth. In case of contact with eyes, rinse thoroughly with water. Stop use and ask a doctor if irritation or rash occurs. These may be signs of serious condition.

Purpose Section

Purpose

Antiseptic

Active Ingredient

Active Ingredients

Ethyl Alcohol 86%vv

Corona Plus Package Label

3.78 ml Corona Plus Product Lable - NDC - 79441-299-01

Front and Back